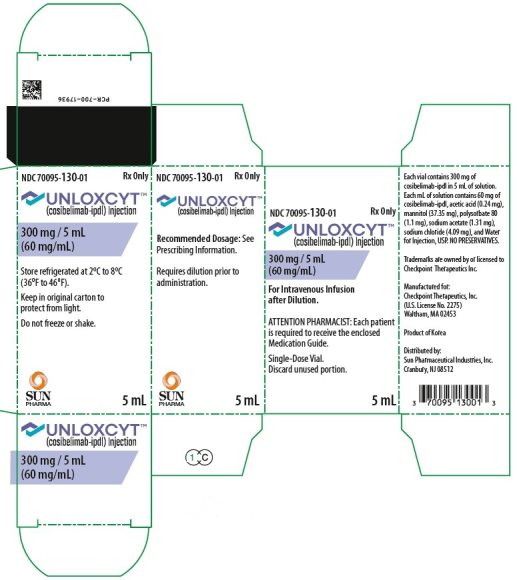 DRUG LABEL: UNLOXCYT
NDC: 70095-130 | Form: INJECTION, SOLUTION
Manufacturer: Sun Pharmaceutical Industries, Inc.
Category: prescription | Type: HUMAN PRESCRIPTION DRUG LABEL
Date: 20251208

ACTIVE INGREDIENTS: cosibelimab 300 mg/5 mL
INACTIVE INGREDIENTS: SODIUM ACETATE 6.55 mg/5 mL; ACETIC ACID 1.2 mg/5 mL; MANNITOL 186.8 mg/5 mL; SODIUM CHLORIDE 20.5 mg/5 mL; POLYSORBATE 80 5.5 mg/5 mL; Water

HIGHLIGHTS OF PRESCRIBING INFORMATION

These highlights do not include all the information needed to use UNLOXCYT safely and effectively. See full prescribing information for UNLOXCYT.
UNLOXCYT (cosibelimab-ipdl) injection, for intravenous use
Initial U.S. Approval: 2024

1. INDICATIONS AND USAGE

UNLOXCYT is a programmed death ligand-1 (PD-L1) blocking antibody indicated for the treatment of adults with metastatic cutaneous squamous cell carcinoma (mCSCC) or locally advanced CSCC (laCSCC) who are not candidates for curative surgery or curative radiation.

2. DOSAGE AND ADMINISTRATION

The recommended dosage of UNLOXCYT is 1,200 mg as an intravenous infusion over 60 minutes every 3 weeks. (2.1)

3. DOSAGE FORMS AND STRENGTHS

Injection: 300 mg/5 mL (60 mg/mL) solution in a single-dose vial. (3)

4. CONTRAINDICATIONS

None. (4)

5. WARNINGS AND PRECAUTIONS

- Immune-Mediated Adverse Reactions (5.1)
  - Immune-mediated adverse reactions can occur in any organ system or tissue, including the following: immune-mediated pneumonitis, immune-mediated colitis, immune-mediated hepatitis, immune-mediated endocrinopathies, immune-mediated dermatologic adverse reactions, immune-mediated nephritis and renal dysfunction, and solid organ transplant rejection.
  - Monitor for early identification and management. Evaluate liver enzymes, creatinine, and thyroid function at baseline and periodically during treatment.
  - Withhold or permanently discontinue UNLOXCYT based on the severity of reaction. (2.2)

- Infusion-Related Reactions: Interrupt, slow the rate of infusion, or permanently discontinue based on severity of reaction. (2.2, 5.2)
- Complications of Allogeneic Hematopoietic Stem Cell Transplantation (HSCT): Fatal and other serious complications can occur in patients who receive allogeneic HSCT before or after being treated with a PD-1/PD-L1 blocking antibody. (5.3)
- Embryo-Fetal Toxicity: Can cause fetal harm. Advise females of reproductive potential of the potential risk to a fetus and to use effective contraception. (5.4, 8.1, 8.3)

6. ADVERSE REACTIONS

The most common adverse reactions (≥10%) were fatigue, musculoskeletal pain, rash, diarrhea, hypothyroidism, constipation, nausea, headache, pruritus, edema, localized infection, and urinary tract infection. (6.1)

To report SUSPECTED ADVERSE REACTIONS, contact Sun Pharmaceutical Industries, Inc. at 1-800- 818-4555 or FDA at 1-800-FDA-1088 or www.fda.gov/medwatch.

8. USE IN SPECIFIC POPULATIONS

Lactation: Advise not to breastfeed. (8.2)

FULL PRESCRIBING INFORMATION

1. INDICATIONS AND USAGE

UNLOXCYT is indicated for the treatment of adults with metastatic cutaneous squamous cell carcinoma (mCSCC) or locally advanced CSCC (laCSCC) who are not candidates for curative surgery or curative radiation.

2. DOSAGE AND ADMINISTRATION

2.1. Recommended Dosage

The recommended dosage of UNLOXCYT is 1,200 mg administered as an intravenous infusion over 60 minutes every 3 weeks until disease progression or unacceptable toxicity.

2.2. Dose Modifications for Adverse Reactions

No dose reductions of UNLOXCYT are recommended. In general, withhold UNLOXCYT for severe (Grade 3) immune-mediated adverse reactions. Permanently discontinue UNLOXCYT for life-threatening (Grade 4) immune-mediated adverse reactions, recurrent severe (Grade 3) immune-mediated reactions that require systemic immunosuppressive treatment, or an inability to reduce corticosteroid dose to a prednisone equivalent of 10 mg or less per day within 12 weeks of initiating steroids.

Dosage modifications for UNLOXCYT for adverse reactions that require management different from these general guidelines are summarized in Table 1.

Table 1: Recommended Dose Modifications for Adverse Reactions
Adverse Reaction | Severity [Based on National Cancer Institute Common Terminology Criteria for Adverse Events (CTCAE), Version 5.] | UNLOXCYT Dosage Modifications
Immune-Mediated Adverse Reactions [see Warnings and Precautions (5.1)]
Pneumonitis | Grade 2 | Withhold [Resume in patients with complete or partial resolution (Grade 0 to 1) after corticosteroid taper. Permanently discontinue if no complete or partial resolution within 12 weeks of initiating steroids or inability to reduce corticosteroid to a prednisone equivalent of 10 mg/day or less within 12 weeks of initiating steroids.]
Pneumonitis | Grade 3 or 4 | Permanently discontinue
Colitis | Grade 2 or 3 | Withhold
Colitis | Grade 4 | Permanently discontinue
Hepatitis with no tumor involvement of the liver | AST or ALT increases to more than 3 and up to 8 times ULN or Total bilirubin increases to more than 1.5 and up to 3 times ULN | Withhold
Hepatitis with no tumor involvement of the liver | AST or ALT increases to more than 8 times ULN or Total bilirubin increases to more than 3 times ULN | Permanently discontinue
Hepatitis with tumor involvement of the liver [If AST and ALT are less than or equal to ULN at baseline in patients with liver involvement, withhold or permanently discontinue UNLOXCYT based on recommendations for hepatitis with no tumor involvement of the liver.] | Baseline AST or ALT is more than 1 and up to 3 times ULN and increases to more than 5 and up to 10 times ULN or Baseline AST or ALT is more than 3 and up to 5 times ULN and increases to more than 8 and up to 10 times ULN | Withhold
Hepatitis with tumor involvement of the liver [If AST and ALT are less than or equal to ULN at baseline in patients with liver involvement, withhold or permanently discontinue UNLOXCYT based on recommendations for hepatitis with no tumor involvement of the liver.] | AST or ALT increases to more than 10 times ULN or Total bilirubin increases to more than 3 times ULN | Permanently discontinue
Endocrinopathies [Depending on clinical severity, consider withholding for Grade 2 endocrinopathy until symptom improvement with hormone replacement. Resume once acute symptoms have resolved.] | Grade 3 or 4 | Withhold until clinically stable or permanently discontinue, depending on severity
Nephritis with renal dysfunction | Grade 2 or 3 increased blood creatinine | Withhold
Nephritis with renal dysfunction | Grade 4 increased blood creatinine | Permanently discontinue
Exfoliative dermatologic conditions | Suspected SJS, TEN, or DRESS | Withhold
Exfoliative dermatologic conditions | Confirmed SJS, TEN, or DRESS | Permanently discontinue
Myocarditis | Grade 2, 3 or 4 | Permanently discontinue
Neurological toxicities | Grade 2 | Withhold
Neurological toxicities | Grade 3 or 4 | Permanently discontinue
Other Adverse Reactions
Infusion-related reactions [see Warnings and Precautions (5.2)] | Grade 1 or 2 | Interrupt or slow the rate of infusion
Infusion-related reactions [see Warnings and Precautions (5.2)] | Grade 3 or 4 | Permanently discontinue
ALT = alanine aminotransferase; AST = aspartate aminotransferase; DRESS: drug rash with eosinophilia and systemic symptoms; SJS: Stevens-Johnson Syndrome; TEN: toxic epidermal necrolysis; ULN: upper limit of normal.

2.3. Preparation and Administration

Visually inspect the vial for particulate matter and discoloration. UNLOXCYT is clear to opalescent, colorless to yellow or slightly brown. Discard the vial if visible particles are observed.

Do not shake the vial.

Preparation for Intravenous Infusion:

- Add 20 mL (1,200 mg) of UNLOXCYT to a 250 mL intravenous infusion bag containing 0.9% Sodium Chloride Injection. UNLOXCYT is compatible with an infusion bag made of polyolefin or polyvinyl chloride.
- Mix diluted solution by gentle inversion. Do not shake.
- Discard any unused portion left in the vial.

Storage of Infusion Solution:

The prepared infusion solution may be stored either:

- At room temperature up to 25°C (77°F) for no more than 24 hours from the time of preparation until the end of infusion.
- Under refrigeration at 2°C to 8°C (36°F to 46°F) for no more than 24 hours from time of preparation until end of infusion. If refrigerated, allow the diluted solution to come to room temperature prior to administration.
- Discard after 24 hours.
- Do not freeze.

Administration:

- Visually inspect the infusion bag for particulate matter and discoloration prior to administration. Discard if the solution is discolored or contains particulate matter.
- Administer by intravenous infusion over 60 minutes through an intravenous line containing a sterile, in-line or add-on of 0.2-micron to 0.22-micron filter.
- Do not administer UNLOXCYT as an intravenous push or bolus injection.
- Do not co-administer other drugs through the same infusion line.

3. DOSAGE FORMS AND STRENGTHS

Injection: 300 mg/5 mL (60 mg/mL), clear to opalescent, colorless to yellow or slightly brown solution in a single-dose vial.

4. CONTRAINDICATIONS

None.

5. WARNINGS AND PRECAUTIONS

5.1. Severe and Fatal Immune-Mediated Adverse Reactions

UNLOXCYT is a monoclonal antibody that belongs to a class of drugs that bind to either the programmed death receptor-1 (PD-1) or PD-ligand 1 (PD-L1), blocking the PD-1/PD-L1 pathway, thereby removing inhibition of the immune response, potentially breaking peripheral tolerance and inducing immune-mediated adverse reactions. Important immune-mediated adverse reactions listed in WARNINGS AND PRECAUTIONS may not include all possible severe and fatal immune-mediated reactions.

Immune-mediated adverse reactions, which can be severe or fatal, can occur in any organ system or tissue. Immune-mediated adverse reactions can occur at any time after starting a PD-1/PD-L1–blocking antibody. While immune-mediated adverse reactions usually manifest during treatment with PD-1/PD-L1–blocking antibodies, they can also manifest after discontinuation of PD-1/PD-L1–blocking antibodies. Immune-mediated adverse reactions affecting more than one body system can occur simultaneously.

Early identification and management of immune-mediated adverse reactions are essential to ensure safe use of PD-1/PD-L1–blocking antibodies. Monitor closely for symptoms and signs that may be clinical manifestations of underlying immune-mediated adverse reactions. Evaluate liver enzymes, creatinine, and thyroid function tests at baseline and periodically during treatment. In cases of suspected immune-mediated adverse reactions, initiate appropriate workup to exclude alternative etiologies, including infection. Institute medical management promptly, including specialty consultation as appropriate.

Withhold or permanently discontinue UNLOXCYT depending on severity [see Dosage and Administration (2.2)]. In general, if UNLOXCYT requires interruption or discontinuation, administer systemic corticosteroids (1 to 2 mg/kg/day prednisone or equivalent) until improvement to Grade 1 or less. Upon improvement to Grade 1 or less, initiate corticosteroid taper and continue to taper over at least 1 month. Consider administration of other systemic immunosuppressants in patients whose immune-mediated adverse reaction is not controlled with corticosteroids.

Toxicity management guidelines for adverse reactions that do not necessarily require systemic steroids (e.g., endocrinopathies, dermatologic reactions) are discussed below.

Immune-Mediated Pneumonitis

UNLOXCYT can cause immune-mediated pneumonitis. In patients treated with other PD-1/PD-L1–blocking antibodies, the incidence of pneumonitis is higher in patients who have received prior thoracic radiation.

Immune-mediated pneumonitis occurred in 1% (3/223, Grade 2) of patients receiving UNLOXCYT. Pneumonitis led to withholding of UNLOXCYT in 0.4% (1/223) of patients. All 3 patients required systemic corticosteroids and pneumonitis did not resolve. One patient in whom UNLOXCYT was withheld for pneumonitis, had UNLOXCYT reinitiated after symptom improvement and had recurrence of pneumonitis.

Immune-Mediated Colitis

UNLOXCYT can cause immune-mediated colitis, which may present with diarrhea, abdominal pain, and lower gastrointestinal (GI) bleeding. Cytomegalovirus infection/reactivation has occurred in patients with corticosteroid-refractory immune-mediated colitis treated with PD-1/PD-L1–blocking antibodies. In cases of corticosteroid-refractory colitis, consider repeating infectious workup to exclude alternative etiologies.

Immune-mediated colitis occurred in 0.4% (1/223, Grade 1) of patients receiving UNLOXCYT. Systemic corticosteroids were required in the patient experiencing colitis. The event of colitis did not resolve, and UNLOXCYT was not reinitiated.

Immune-Mediated Hepatitis

UNLOXCYT can cause immune-mediated hepatitis, defined as requiring the use of systemic corticosteroids and the absence of a clear alternate etiology.

Immune-Mediated Endocrinopathies

Adrenal Insufficiency

UNLOXCYT can cause primary or secondary adrenal insufficiency. For Grade 2 or higher adrenal insufficiency, initiate symptomatic treatment per institutional guidelines, including hormone replacement as clinically indicated. Withhold or permanently discontinue UNLOXCYT depending on severity [see Dosage and Administration (2.2)].

Adrenal insufficiency occurred in 0.9% (2/223) of patients receiving UNLOXCYT, including Grade 2 in 0.4% (1/223) of patients. UNLOXCYT was withheld for adrenal insufficiency in one of these patients and was reinitiated after symptom improvement. Systemic corticosteroids were required in both patients with adrenal insufficiency.

Hypophysitis

UNLOXCYT can cause immune-mediated hypophysitis. Hypophysitis can present with acute symptoms associated with mass effect such as headache, photophobia, or visual field cuts. Hypophysitis can cause hypopituitarism. Initiate hormone replacement as clinically indicated. Withhold or permanently discontinue UNLOXCYT depending on severity [see Dosage and Administration (2.3)].

Thyroid Disorders

UNLOXCYT can cause immune-mediated thyroid disorders. Thyroiditis can present with or without endocrinopathy. Hypothyroidism can follow hyperthyroidism. Initiate hormone replacement or medical management of hyperthyroidism as clinically indicated. Withhold or permanently discontinue UNLOXCYT depending on severity [see Dosage and Administration (2.2)].

Hypothyroidism: Hypothyroidism occurred in 10% (22/223) of patients receiving UNLOXCYT, including Grade 2 in 5% (10/223) of patients. Hypothyroidism resolved in 7 of the 22 patients.

Hyperthyroidism: Hyperthyroidism occurred in 5% (12/223) of patients receiving UNLOXCYT, including Grade 2 in 0.4% (1/223) of patients. Hyperthyroidism resolved in 10 of the 12 patients.

Type 1 Diabetes Mellitus, which can present with diabetic ketoacidosis

UNLOXCYT can cause type 1 diabetes mellitus, which can present with diabetic ketoacidosis. Monitor patients for hyperglycemia or other signs and symptoms of diabetes. Initiate treatment with insulin as clinically indicated. Withhold or permanently discontinue UNLOXCYT depending on severity [see Dosage and Administration (2.2)].

Immune-Mediated Nephritis with Renal Dysfunction

UNLOXCYT can cause immune-mediated nephritis, defined as the required use of systemic corticosteroids or other immunosuppressants and the absence of a clear alternate etiology.

Immune-Mediated Dermatologic Adverse Reactions

UNLOXCYT can cause immune-mediated rash or dermatitis. Bullous and exfoliative dermatitis, including Stevens-Johnson syndrome (SJS), toxic epidermal necrolysis (TEN), and drug rash with eosinophilia and systemic symptoms (DRESS), have occurred with PD-1/PD-L1–blocking antibodies. Topical emollients and/or topical corticosteroids may be adequate to treat mild to moderate non-bullous/exfoliative rashes. Withhold or permanently discontinue UNLOXCYT depending on severity [see Dosage and Administration (2.2)].

Immune-mediated dermatologic adverse reactions occurred in 7% (15/223) of patients receiving UNLOXCYT, including Grade 3 in 0.9% (2/223) of patients and Grade 2 in 4% (9/223) of patients. Dermatologic adverse reactions led to permanent discontinuation of UNLOXCYT in 0.4% (1/223) of patients and withholding of UNLOXCYT in 0.9% (2/223) of patients. Systemic corticosteroids were required in 33% (5/15) of patients with dermatologic adverse reactions. Dermatologic adverse reactions resolved in 7 of the 15 patients. Of the 2 patients in whom UNLOXCYT was withheld for dermatologic adverse reactions, 1 patient reinitiated UNLOXCYT after symptom improvement and had recurrence of the dermatologic adverse reaction, which resolved after UNLOXCYT was withheld a second time.

Other Immune-Mediated Adverse Reactions

The following clinically significant immune-mediated adverse reactions occurred in <1% of the 223 patients who received UNLOXCYT [see Adverse Reactions (6.1)] or were reported with the use of other PD-1/PD-L1–blocking antibodies. Severe or fatal cases have been reported for some of these adverse reactions.

Cardiac/Vascular: Myocarditis, pericarditis, vasculitis.

Nervous System: Meningitis, encephalitis, myelitis and demyelination, myasthenic syndrome/myasthenia gravis (including exacerbation), Guillain-Barre syndrome, nerve paresis, autoimmune neuropathy.

Ocular: Uveitis, iritis, other ocular inflammatory toxicities. Some cases can be associated with retinal detachment. Various grades of visual impairment to include blindness can occur. If uveitis occurs in combination with other immune-mediated adverse reactions, consider a Vogt-Koyanagi-Harada–like syndrome, as this may require treatment with systemic steroids to reduce the risk of permanent vision loss.

Gastrointestinal: Pancreatitis, including increases in serum amylase and lipase levels, gastritis, duodenitis.

Musculoskeletal and Connective Tissue: Myositis/polymyositis, rhabdomyolysis and associated sequelae including renal failure, arthritis, polymyalgia rheumatica.

Endocrine: Hypoparathyroidism.

Other (Hematologic/Immune): Autoimmune hemolytic anemia, aplastic anemia, hemophagocytic lymphohistiocytosis, systemic inflammatory response syndrome, histiocytic necrotizing lymphadenitis (Kikuchi lymphadenitis), sarcoidosis, immune thrombocytopenia, solid organ transplant rejection, other transplant (including corneal graft) rejection.

5.2. Infusion-Related Reactions

UNLOXCYT can cause severe or life-threatening infusion-related reactions. Infusion-related infusion reactions were reported in 11% (24/223) of patients, including Grade 2 in 5.8% (13/223) of patients receiving UNLOXCYT.

Monitor patients for signs and symptoms of infusion-related reactions. Interrupt or slow the rate of infusion or permanently discontinue UNLOXCYT based on severity of reaction [see Dosage and Administration (2.2)]. Consider premedication with an antipyretic and/or an antihistamine for patients who have had previous systemic reactions to infusions of therapeutic proteins.

5.3. Complications of Allogeneic HSCT

Fatal and other serious complications can occur in patients who receive allogeneic hematopoietic stem cell transplantation (HSCT) before or after being treated with a PD-1/PD-L1–blocking antibody. Transplant-related complications include hyperacute graft-versus-host disease (GVHD), acute GVHD, chronic GVHD, hepatic veno-occlusive disease after reduced intensity conditioning, and steroid-requiring febrile syndrome (without an identified infectious cause). These complications may occur despite intervening therapy between PD-1/PD-L1 blockade and allogeneic HSCT.

Follow patients closely for evidence of transplant-related complications and intervene promptly. Consider the benefit versus risks of treatment with a PD-1/PD-L1–blocking antibody prior to or after an allogeneic HSCT.

5.4. Embryo-Fetal Toxicity

Based on its mechanism of action, UNLOXCYT can cause fetal harm when administered to a pregnant woman. Animal studies have demonstrated that inhibition of the PD-1/PD-L1 pathway can lead to increased risk of immune-mediated rejection of the developing fetus, resulting in fetal death. Advise pregnant women of the potential risk to a fetus. Advise females of reproductive potential to use effective contraception during treatment with UNLOXCYT and for 4 months after the last dose [see Use in Specific Populations (8.1, 8.3)].

6. ADVERSE REACTIONS

The following clinically significant adverse reactions are described elsewhere in the labeling:

- Severe and fatal immune-mediated adverse reactions [see Warnings and Precautions (5.1)]
- Infusion-related reactions [see Warnings and Precautions (5.2)]
- Complications of Allogeneic HSCT [see Warnings and Precautions (5.3)]

6.1. Clinical Trials Experience

Because clinical trials are conducted under widely varying conditions, adverse reaction rates observed in the clinical trials of a drug cannot be directly compared with rates in the clinical trials of another drug and may not reflect the rates observed in practice.

The pooled safety population described in WARNINGS AND PRECAUTIONS reflects exposure to UNLOXCYT as a single agent in 223 patients in two open-label, single-arm, multicohort studies, including 141 patients with advanced CSCC and 82 patients with other solid tumors and hematologic malignancies. UNLOXCYT was administered intravenously at doses of 800 mg every 2 weeks (n=174), 1,200 mg every 3 weeks (n=35), or other doses (n=14). Among the 223 patients, 54% were exposed for ≥24 weeks and 17% were exposed for ≥72 weeks.

The safety of UNLOXCYT was evaluated in Study CK-301-101 in 141 patients with metastatic or locally advanced disease CSCC [see Clinical Studies (14)]. Patients received UNLOXCYT 800 mg every 2 weeks (n=115) or 1,200 mg every 3 weeks (n=26) as an intravenous infusion until disease progression or unacceptable toxicity. The median duration of exposure was 36 weeks (2 weeks to 3.7 years).

Serious adverse reactions occurred in 31% of advanced patients with CSCC who received UNLOXCYT. The most frequent serious adverse reactions (≥ 2% of patients) were sepsis (2.8%), pneumonia (2.8%) and pyrexia (2.1%).

Permanent discontinuation of UNLOXCYT due to an adverse reaction occurred in 8% of patients. Adverse reactions resulting in permanent discontinuation of UNLOXCYT were COVID-19, COVID-19 pneumonia, sepsis, ulcerative keratitis, tumor thrombosis, axillary pain, paresthesia, cholestasis, hepatic cytolysis, wound hemorrhage, neck pain, pemphigoid, and eye pain (1 patient each).

Dosage interruptions due to an adverse reaction occurred in 36% of patients who received UNLOXCYT. The adverse reaction that required dosage interruption in ≥ 2% of patients who received UNLOXCYT was COVID-19 (2%).

The most common (≥ 10%) adverse reactions were fatigue, musculoskeletal pain, rash, diarrhea, hypothyroidism, constipation, nausea, headache, pruritus, edema, localized infection, and urinary tract infection.

Table 2 and Table 3 summarize adverse reactions and laboratory abnormalities, respectively in CK-301-101.

Table 2: Adverse Reactions in ≥ 10% of Patients with Metastatic or Locally Advanced CSCC Receiving UNLOXCYT in Study CK-301-101
 | UNLOXCYT N = 141 %
System Organ Class Preferred Term | All Grades % | Grade 3 or 4 %
General disorders and administrative site conditions
Fatigue [Represents a composite of multiple related terms] | 33 | 3
Edema | 11 | 0
Musculoskeletal and connective tissue disorders
Musculoskeletal pain | 25 | 3
Skin and subcutaneous tissue disorders
Rash | 23 | 1
Pruritus | 12 | 0
Endocrine disorder
Hypothyroidism | 14 | 0
Gastrointestinal disorders
Diarrhea | 14 | 0
Nausea | 13 | 0
Constipation | 13 | 0
Nervous system disorders
Headache | 12 | 0
Infections and infestations
Localized infection | 10 | 0.7
Urinary tract infection | 10 | 0
Toxicity was graded per National Cancer Institute Common Terminology Criteria for Adverse Events (NCI CTCAE) v.4.03 (or later version)

Table 3: Laboratory Abnormalities that Worsened from Baseline to Grade 3 or 4 Occurring in ≥ 1% of Patients with Metastatic or Locally Advanced CSCC Receiving UNLOXCYT in Study CK-301-101
Laboratory Abnormality | UNLOXCYT (N = 141)
Laboratory Abnormality | All Grades % [The denominator used to calculate the rate varied from 122-140 based on the number of patients with a baseline value and at least one post-treatment value.] | Grade 3 or 4 %
Hematology
Hemoglobin decreased | 45 | 4
Lymphocytes decreased | 41 | 6
Platelets decreased | 14 | 1
Leukocytes decreased | 10 | 1
Chemistry
Sodium decreased | 38 | 5
Alkaline phosphatase increased | 26 | 1
Alanine transferase increased | 25 | 4
Lipase increased | 25 | 3
Aspartate transaminase increased | 24 | 3
Potassium increased | 23 | 3
Calcium increased | 14 | 2
Toxicity graded per NCI CTCAE v5

8. USE IN SPECIFIC POPULATIONS

8.1. Pregnancy

Risk Summary

Based on its mechanism of action, UNLOXCYT can cause fetal harm when administered to a pregnant woman [see Clinical Pharmacology (12.1)]. There are no available data on the use of UNLOXCYT in pregnant women. Animal studies have demonstrated that inhibition of the PD-1/PD-L1 pathway can lead to increased risk of immune-mediated rejection of the developing fetus resulting in fetal death (see Data). Human IgG1 immunoglobulins (IgG1) are known to cross the placental barrier; therefore, cosibelimab-ipdl has the potential to be transmitted from the mother to the developing fetus. Advise women of the potential risk to a fetus.

In the U.S. general population, the estimated background risk of major birth defects and miscarriage in clinically recognized pregnancies is 2% to 4% and 15% to 20%, respectively.

Data

Animal Data: Animal reproduction studies have not been conducted with cosibelimab-ipdl to evaluate its effect on reproduction and fetal development. A central function of the PD-1/PD-L1 pathway is to preserve pregnancy by maintaining maternal immune tolerance to the fetus. In murine models of pregnancy, blockade of PD-L1 signaling has been shown to disrupt tolerance to the fetus and to result in an increase in fetal loss; therefore, potential risks of administering UNLOXCYT during pregnancy include increased rates of abortion or stillbirth. As reported in the literature, there were no malformations related to the blockade of PD-1/PD-L1 signaling in the offspring of these animals; however, immune-mediated disorders occurred in PD-1 and PD-L1 knockout mice. Based on its mechanism of action, fetal exposure to UNLOXCYT may increase the risk of developing immune-mediated disorders or altering the normal immune response.

8.2. Lactation

Risk Summary

There is no information regarding the presence of cosibelimab-ipdl in human milk or its effects on the breastfed child or on milk production. Because of the potential for serious adverse reactions in a breastfed child, advise women not to breastfeed during treatment and for 4 months after the last dose of UNLOXCYT.

8.3. Females and Males of Reproductive Potential

UNLOXCYT can cause fetal harm when administered to a pregnant woman [see Use in Specific Populations (8.1)].

Pregnancy Testing

Verify pregnancy status in females of reproductive potential prior to initiating UNLOXCYT [see Use in Specific Populations (8.1)].

Contraception

Females: Advise females of reproductive potential to use effective contraception during treatment with UNLOXCYT and for 4 months after the last dose.

8.4. Pediatric Use

The safety and effectiveness of UNLOXCYT have not been established in pediatric patients.

8.5. Geriatric Use

Of the 141 patients treated with UNLOXCYT as a single agent, 21% (29) were younger than 65 years, 31% (44) were aged 65 through 75 years, and 48% (68) were 75 years or older. No overall differences in safety or effectiveness were observed between these patients and younger patients.

11. DESCRIPTION

Cosibelimab-ipdl is a human programmed death ligand-1 (PD-L1) blocking antibody. Cosibelimab-ipdl is a human IgG1 lambda monoclonal antibody. Cosibelimab-ipdl is produced in Chinese hamster ovary (CHO) cells and has a calculated molecular weight of approximately 147 kDa.

UNLOXCYT (cosibelimab-ipdl) injection for intravenous use is a sterile, preservative-free, clear to opalescent, colorless to yellow or slightly brown solution. It is supplied in single-dose vials.

Each vial contains 300 mg of UNLOXCYT in 5 mL of solution with a pH of 5.3. Each mL of solution contains 60 mg of cosibelimab-ipdl, acetic acid (0.24 mg), mannitol (37.35 mg), polysorbate 80 (1.1 mg), sodium acetate (1.31 mg), sodium chloride (4.09 mg), and Water for Injection, USP.

12. CLINICAL PHARMACOLOGY

12.1. Mechanism of Action

PD-L1 may be expressed on tumor cells and tumor-infiltrating immune cells and can contribute to the inhibition of the anti-tumor immune response in the tumor microenvironment. Binding of PD-L1 to the PD-1 and B7.1 receptors found on T cells and antigen presenting cells suppresses cytotoxic T-cell activity, T-cell proliferation, and cytokine production. Cosibelimab-ipdl binds PD-L1 and blocks the interaction between PD-L1 and its receptors PD-1 and B7.1. This interaction releases the inhibitory effects of PD-L1 on the anti-tumor immune response. Cosibelimab-ipdl has also been shown to induce antibody-dependent cell-mediated cytotoxicity (ADCC) in vitro.

12.2. Pharmacodynamics

Cosibelimab-ipdl exposure-response relationships and the time course of pharmacodynamic responses have not been fully characterized.

12.3. Pharmacokinetics

Cosibelimab-ipdl pharmacokinetic parameters are presented as geometric mean (coefficient of variation) unless otherwise stated. At the recommended dosage, the cosibelimab-ipdl steady-state maximum plasma concentration (Cmax) is 492 µg/mL (24.3%) and area under curve (AUC) is 112000 µg*h/mL (39.6%). Cosibelimab-ipdl Cmax and AUC increased proportionally over the dose range of 800 mg to 1,200 mg following single dosing. Steady-state concentrations of cosibelimab-ipdl are reached by 12 weeks.

At 1,200 mg every 3 weeks, the mean cosibelimab-ipdl concentrations (coefficient of variation, CV%) at steady-state ranged between a minimum concentration of 120 µg/L (46.3%) and a maximum concentration of 453 µg/L (22.2%). Steady-state exposure was achieved after 84 days of treatment.

In patients with CSCC, cosibelimab-ipdl steady-state exposure at 1,200 mg every 3 weeks (the recommended dosage) was comparable to the exposure at 800 mg every 2 weeks.

Distribution

Cosibelimab-ipdl steady state volume of distribution is approximately 5.67 L (19.7%).

Elimination

Cosibelimab-ipdl steady state elimination half-life is 17.8 days (43.8%), and the clearance is 0.256 L/day (41%).

Specific Populations

No clinically significant differences in the pharmacokinetics of cosibelimab-ipdl were observed based on age (24.8 to 95.0 years), sex, race (79.6% White, 10.7% Asian, 0.5% African American, and 1.5% other), ethnicity (76.9% Not Hispanic/Latino and 4.9% Hispanic/Latino), ADA and nAb status, albumin (22 to 51 g/L), tumor type, tumor diameter, and renal impairment (CLcr 15 mL/min and higher). The effect of severe hepatic impairment (bilirubin > 3 × ULN and any AST) on cosibelimab-ipdl pharmacokinetics is unknown.

12.6 Immunogenicity

The observed incidence of anti-drug antibodies is highly dependent on the sensitivity and specificity of the assay. Differences in assay methods preclude meaningful comparisons of the incidence of anti-drug antibodies in the studies described below with the incidence of anti-drug antibodies in other studies, including those of UNLOXCYT or of other cosibelimab products.

Anti-drug antibody (ADA) and neutralizing antibody (nAb) responses were monitored throughout the treatment period where the benefit to risk ratio was assessed. ADAs were detected in 65/133 (49%) of patients treated with UNLOXCYT and nAbs were detected in 2/65 (3.0%) of the patients. UNLOXCYT-treated patients who developed anti-cosibelimab antibodies had reduced UNLOXCYT concentrations (20% lower compared to UNLOXCYT-treated subjects who did not develop anti-cosibelimab-ipdl antibodies).

There was no clinically significant effect of anti-cosibelimab-ipdl antibodies on the efficacy or safety of cosibelimab-ipdl.

13. NONCLINICAL TOXICOLOGY

13.1. Carcinogenesis, Mutagenesis, Impairment of Fertility

No studies have been performed to assess the potential of cosibelimab-ipdl for carcinogenicity or genotoxicity.

Fertility studies have not been conducted with cosibelimab-ipdl in animals. In 1- and 3-month repeat-dose toxicology studies in monkeys, there were no notable effects in the male and female reproductive organs up to the highest dose tested of 100 mg/kg/dose; however, many animals in these studies were not sexually mature.

13.2. Animal Toxicology and/or Pharmacology

In animal models, inhibition of PD-L1/PD-1 signaling increased the severity of some infections and enhanced inflammatory responses. Mycobacterium tuberculosis-infected PD-1 knockout mice exhibit markedly decreased survival compared with wild-type controls, which correlated with increased bacterial proliferation and inflammatory responses in these animals. PD-L1 and PD-1 knockout mice and mice receiving PD-L1–blocking antibody have also shown decreased survival following infection with lymphocytic choriomeningitis virus.

14. CLINICAL STUDIES

14.1. Cutaneous Squamous Cell Carcinoma (CSCC)

The efficacy of UNLOXCYT was evaluated in Study CK-301-101 (NCT03212404), a multicenter, multicohort, open-label study in patients with metastatic CSCC (mCSCC) or locally advanced CSCC (laCSCC) who were not candidates for curative surgery or curative radiation. Patients were excluded if they had the following: active or suspected autoimmune disease, allogeneic transplant within 6 months prior to treatment, prior treatment with anti–PD-1/PD-L1 blocking antibodies or other immune checkpoint inhibitor therapy, uncontrolled or significant cardiovascular disease, ECOG PS ≥ 2, or infection with HIV, hepatitis B or hepatitis C.

Patients received UNLOXCYT 800 mg every 2 weeks until disease progression or unacceptable toxicity. Tumor response assessments were performed every 8 weeks for the first 8 months and every 12 weeks thereafter.

The major efficacy outcomes were objective response rate (ORR) and duration of response (DOR) as assessed by an independent central review committee (ICR) according to Response Evaluation Criteria in Solid Tumors (RECIST) version 1.1. For patients with laCSCC with externally visible target lesions not assessable by radiologic imaging, ORR was determined by ICR assessments of digital photography (WHO criteria).

The efficacy population consisted of 109 patients. The median age was 75 years (range 37-95); 78% were ≥ 65 years; 72% were male; 85% were White; 6% were Asian; 1% were Black or African American; 7% were race unknown or missing; 34% had ECOG performance status of 0, and 66% had ECOG performance score of 1. Seven percent of patients received at least one prior anti-cancer systemic therapy, 66% of patients had prior surgery, and 69% of patients had prior radiotherapy. Efficacy results are summarized in Table 4.

Table 4: Efficacy Results for Study CK-301-101
Efficacy Endpoints | mCSCC; N = 78 | laCSCC; N = 31
Objective Response Rate (ORR)
ORR, n (%); (95% CI) | 39 (50); (38, 62) | 17 (55); (36, 73)
Complete response, n (%) | 10 (13) | 8 (26)
Partial response, n (%) | 29 (37) | 9 (29)
Duration of Response (DOR)a
Number of responders | N=39 | N=17
Median DOR in monthsb (Range) | NR (1.4+, 45.3+) | NR (8.3, 31.3+)
Responders with observed DOR ≥ 6 months, n (%)c | 33 (85) | 17 (100)
Responders with observed DOR ≥ 12 months, n (%)c | 26 (67) | 15 (88)

CI: confidence interval; NR: not reached; +: Denotes ongoing at last assessment.

a Median follow up time: mCSCC: 29.3 months; laCSCC: 24.1 months.

b Based on Kaplan-Meier estimate.

c The numerator includes the number of patients whose observed DOR reached at least the specified times of 6 or 12 months. Patients who did not have the opportunity to reach the specified timepoint were included in the denominator only.

16. HOW SUPPLIED/STORAGE AND HANDLING

UNLOXCYT (cosibelimab-ipdl) injection is a clear to opalescent, colorless to yellow or slightly brown solution supplied in a carton containing one 300 mg/5 mL (60 mg/mL), single-dose vial (NDC 70095-130-01).

STORAGE AND HANDLING

Store in a refrigerator at 2°C to 8°C (36°F to 46°F) in original carton to protect from light.

Do not freeze or shake.

17. PATIENT COUNSELING INFORMATION

Advise the patient to read the FDA-approved patient labeling (Medication Guide).

Immune-Mediated Adverse Reactions

Advise patients that UNLOXCYT can cause immune-mediated adverse reactions that may require corticosteroid treatment and interruption or discontinuation of UNLOXCYT including the following [see Warnings and Precautions (5.1)]:

- Pneumonitis: Advise patients to contact their healthcare provider immediately for signs or symptoms of pneumonitis, including new or worsening symptoms of cough, chest pain, or shortness of breath.
- Colitis: Advise patients to contact their healthcare provider immediately for signs or symptoms of colitis, including diarrhea, blood or mucus in stools, or severe abdominal pain.
- Hepatitis: Advise patients to contact their healthcare provider immediately for signs or symptoms of hepatitis.
- Endocrinopathies: Advise patients to contact their healthcare provider immediately for signs or symptoms of hypothyroidism, hyperthyroidism, adrenal insufficiency, hypophysitis, or type 1 diabetes mellitus.
- Nephritis: Advise patients to contact their healthcare provider immediately for signs or symptoms of nephritis.
- Dermatologic Adverse Reactions: Advise patients to contact their healthcare provider immediately if they develop a new rash.
- Other Immune-Mediated Adverse Reactions:
  - Advise patients that immune-mediated adverse reactions can occur and may involve any organ system, and to contact their healthcare provider immediately for any new signs or symptoms [see Warnings and Precautions (5.1)].
  - Advise patients of the risk of solid organ transplant rejection and other transplant (including corneal graft) rejection. Advise patients to contact their healthcare provider immediately for signs or symptoms of organ transplant (including corneal graft) rejection [see Warnings and Precautions (5.1)].

Infusion-Related Reactions

Advise patients to contact their healthcare provider immediately for signs or symptoms of infusion-related reactions [see Warnings and Precautions (5.2)].

Complications of Allogeneic HSCT or Solid Organ Transplant Rejection

Advise patients to contact their healthcare provider immediately if they develop signs or symptoms of post-allogeneic HSCT complications or of solid organ transplant rejection [see Warnings and Precautions (5.1, 5.3)].

Embryo-Fetal Toxicity

- Advise females of reproductive potential that UNLOXCYT can cause harm to a fetus and to inform their healthcare provider of a known or suspected pregnancy [see Warnings and Precautions (5.4) and Use in Specific Populations (8.1, 8.3)].
- Advise females of reproductive potential to use effective contraception during treatment with UNLOXCYT and for 4 months after the last dose [see Use in Specific Populations (8.3)].

Lactation

- Advise female patients not to breastfeed during treatment with UNLOXCYT and for 4 months after the last dose [see Use in Specific Populations (8.2)].

Trademarks are owned by or licensed to Checkpoint Therapeutics, Inc.

Manufactured for:

Checkpoint Therapeutics, Inc.

Waltham, MA 02453

U.S. License No. 2275

Product of Korea

Distributed by:

Sun Pharmaceutical Industries, Inc.

Cranbury, NJ 08512

©2025 Sun Pharmaceutical Industries, Inc.

All rights reserved

UNLOXCYT is a trademark of Checkpoint Therapeutics, Inc.

Rev. NOV 2025

MEDICATION GUIDE

UNLOXCYT (un-LOX-sit)

(cosibelimab-ipdl)

injection

What is the most important information I should know about UNLOXCYT?

UNLOXCYT is a medicine that may treat a type of skin cancer by working with your immune system. UNLOXCYT can cause your immune system to attack normal organs and tissues in any area of your body and can affect the way they work. These problems can sometimes become severe or life-threatening and can lead to death. You can have more than one of these problems at the same time. These problems may happen anytime during treatment or even after your treatment has ended.

Call or see your healthcare provider right away if you develop any new or worsening signs or symptoms, including:

Lung problems.

- cough

- chest pain
- shortness of breath

Intestinal problems.

- diarrhea (loose stools) or more frequent bowel movements than usual
- stools that are black, tarry, sticky, or have blood or mucus
- severe stomach-area (abdomen) pain or tenderness

Liver problems.

- yellowing of your skin or the whites of your eyes
- severe nausea or vomiting
- pain on the right side of your stomach area (abdomen)

- dark urine (tea colored)
- bleeding or bruising more easily than normal

Hormone gland problems.

- headache that will not go away or unusual headaches
- eye sensitivity to light
- eye problems
- rapid heartbeat
- increased sweating
- extreme tiredness
- weight gain or weight loss
- feeling more hungry or thirsty than usual

- urinating more often than usual
- hair loss
- feeling cold
- constipation
- your voice gets deeper
- dizziness or fainting
- changes in mood or behavior, such as decreased sex drive, irritability, or forgetfulness

Kidney problems:

- decrease in your amount urine
- blood in your urine

- swelling of your ankles
- loss of appetite

Skin problems.

- rash
- itching
- fever or flu-like symptoms
- skin blistering or peeling

- painful sores or ulcers in mouth or nose, throat, or genital area
- swollen lymph nodes

Problems can also happen in other organs and tissues. These are not all of the signs and symptoms of immune system problems that can happen with UNLOXCYT. Call or see your healthcare provider right way for any new or worsening signs or symptoms which may include:

- chest pain, irregular heartbeat, shortness of breath or swelling of ankles
- confusion, sleepiness, memory problems, changes in mood or behavior, stiff neck, balance problems, tingling or numbness of the arms or legs
- double vision, blurry vision, sensitivity to light, eye pain, changes in eyesight
- persistent or severe muscle pain or weakness, muscle cramps
- low red blood cells, bruising

Infusion reactions that can sometimes be severe or life-threatening. Signs and symptoms of infusion reactions may include:

- nausea
- chills or shaking
- itching or rash
- flushing
- shortness of breath or wheezing

- dizziness
- feel like passing out
- fever
- back or neck pain

Rejection of a transplanted organ. Your healthcare provider should tell you what signs and symptoms you should report and monitor you, depending on the type of organ transplant that you have had.

Complications, including graft-versus-host disease (GVHD), in people who have received a bone marrow (stem cell) transplant that uses donor stem cells (allogeneic). These complications can be serious and can lead to death. These complications may happen if you underwent transplantation either before or after being treated with UNLOXCYT. Your healthcare provider will monitor you for these complications.

Getting medical treatment right away may help keep these problems from becoming more serious. Your healthcare provider will check you for these problems during your treatment with UNLOXCYT. Your healthcare provider may treat you with corticosteroid or hormone replacement medicines. Your healthcare provider may also need to delay or completely stop treatment with UNLOXCYT if you have severe side effects.

What is UNLOXCYT?

UNLOXCYT is a prescription medicine used to treat adults with a type of skin cancer called cutaneous squamous cell carcinoma (CSCC). UNLOXCYT may be used to treat CSCC that has spread or cannot be cured by surgery or radiation.

It is not known if UNLOXCYT is safe and effective in children.

Before you receive UNLOXCYT, tell your healthcare provider about all your medical conditions, including if you:

- have immune system problems such as Crohn’s disease, ulcerative colitis, or lupus
- have received an organ transplant, including corneal transplant.
- have received or plan to receive a stem cell transplant that uses donor stem cells (allogeneic)
- have received radiation treatment to your chest area
- have a condition that affects your nervous system, such as myasthenia gravis or Guillain-Barré syndrome.
- are pregnant or plan to become pregnant. UNLOXCYT can harm your unborn baby.

Females who are able to become pregnant:

- Your healthcare provider will give you a pregnancy test before you start treatment with UNLOXCYT.
- You should use an effective method of birth control during your treatment and for 4 months after the last dose of UNLOXCYT. Talk to your healthcare provider about birth control methods that you can use during this time.
- Tell your healthcare provider right away if you become pregnant or think you may be pregnant during treatment with UNLOXCYT.

- are breastfeeding or plan to breastfeed. It is not known if UNLOXCYT passes into your breast milk. Do not breastfeed during treatment and for 4 months after the last dose of UNLOXCYT.

Tell your healthcare provider about all the medicines you take, including prescription and over-the-counter medicines, vitamins, and herbal supplements.

How will I receive UNLOXCYT?

- Your healthcare provider will give you UNLOXCYT into your vein through an intravenous (IV) line over 60 minutes.
- UNLOXCYT is usually given every 3 weeks.
- Your healthcare provider will decide how many treatments you will need.
- Your healthcare provider will do blood tests to check you for side effects.
- If you miss any appointments, call your healthcare provider as soon as possible to reschedule your appointment.

What are the possible side effects of UNLOXCYT?

UNLOXCYT can cause serious side effects.

- See “What is the most important information I should know about UNLOXCYT?”

The most common side effects of UNLOXCYT include tiredness or weakness, muscle or bone pain, rash, diarrhea, low thyroid hormone levels (hypothyroidism), constipation, nausea, headache, itchy skin, swelling, infection, and urinary tract infection.

These are not all the possible side effects of UNLOXCYT.

Call your doctor for medical advice about side effects. You may report side effects to FDA at 1-800-FDA-1088.

General Information about the safe and effective use of UNLOXCYT.

Medicines are sometimes prescribed for purposes other than those listed in a Medication Guide. If you would like more information about UNLOXCYT, talk with your healthcare provider. You can ask your healthcare provider for information about UNLOXCYT that is written for healthcare professionals.

What are the ingredients of UNLOXCYT?

Active Ingredient: cosibelimab-ipdl

Inactive ingredients: acetic acid, mannitol, polysorbate 80, sodium acetate, sodium chloride, and Water for Injection.

Manufactured for: Checkpoint Therapeutics, Inc.,Waltham, MA 02453

U.S. License No. 2275, Product of Korea

Distributed by:

Sun Pharmaceutical Industries, Inc., Cranbury, NJ 08512

© 2025 Sun Pharmaceutical Industries, Inc.

All rights reserved

UNLOXCYT is a trademark of Checkpoint Therapeutics, Inc.

PRINCIPAL DISPLAY PANEL - 5 mL Vial Carton

NDC 70095-130-01
Rx Only

UNLOXCYT™
(cosibelimab-ipdl) Injection

300 mg / 5 mL
(60 mg/mL)

For Intravenous Infusion
after Dilution.

ATTENTION PHARMACIST: Each patient
is required to receive the enclosed
Medication Guide.

Single-Dose Vial.
Discard unused portion.

5 mL